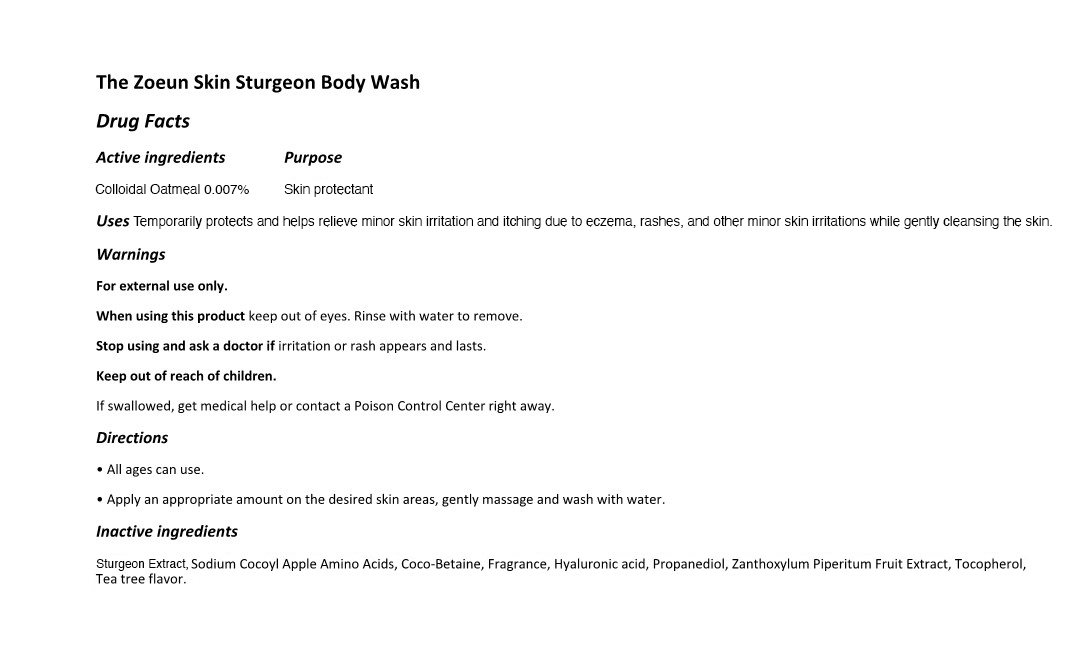 DRUG LABEL: The Zoeun Skin Sturgeon Body Wash
NDC: 83636-119 | Form: LIQUID
Manufacturer: Sturgeonbio Co.,Ltd.
Category: otc | Type: HUMAN OTC DRUG LABEL
Date: 20251001

ACTIVE INGREDIENTS: OATMEAL 0.007 g/100 mL
INACTIVE INGREDIENTS: ZANTHOXYLUM PIPERITUM FRUIT PULP; STURGEON, UNSPECIFIED; SODIUM COCOYL APPLE AMINO ACIDS; COCAMIDOPROPYL BETAINE; MELALEUCA ALTERNIFOLIA (TEA TREE) LEAF OIL; TOCOPHEROL; PROPANEDIOL; FRAGRANCE 13576; HYALURONIC ACID

119 THE ZOEUN SKIN STURGEON BODY WASH

Active Ingredients

Colloidal Oatmeal 0.007%

Purpose

Skin Protectant

Uses

Temporarily protects and helps relieve minor skin irritation and itching due to eczema, rashes, and other minor skin irritations while gently cleansing the skin.

Warnings

- Keep out of reach of children.
- If swallowed, get medical help or contact a Poison Control Center right away.

Warnings

Stop using and ask a doctor if irritation or rash appears and lasts.

Warnings

- When using this product keep out of eyes.
- Rinse with water to remove.

Warnings

For external use only.

Directions

- All ages can use.
- Apply an appropriate amount on the desired skin areas, gently massage and wash with water.

Inactive Ingredients

Sturgeon Extract, Sodium Cocoyl Apple Amino Acids, Coco-Betaine, Fragrance, Hyaluronic acid, Propanediol,
Zanthoxylum Piperitum Fruit Extract, Tocopherol, Tea tree flavor.